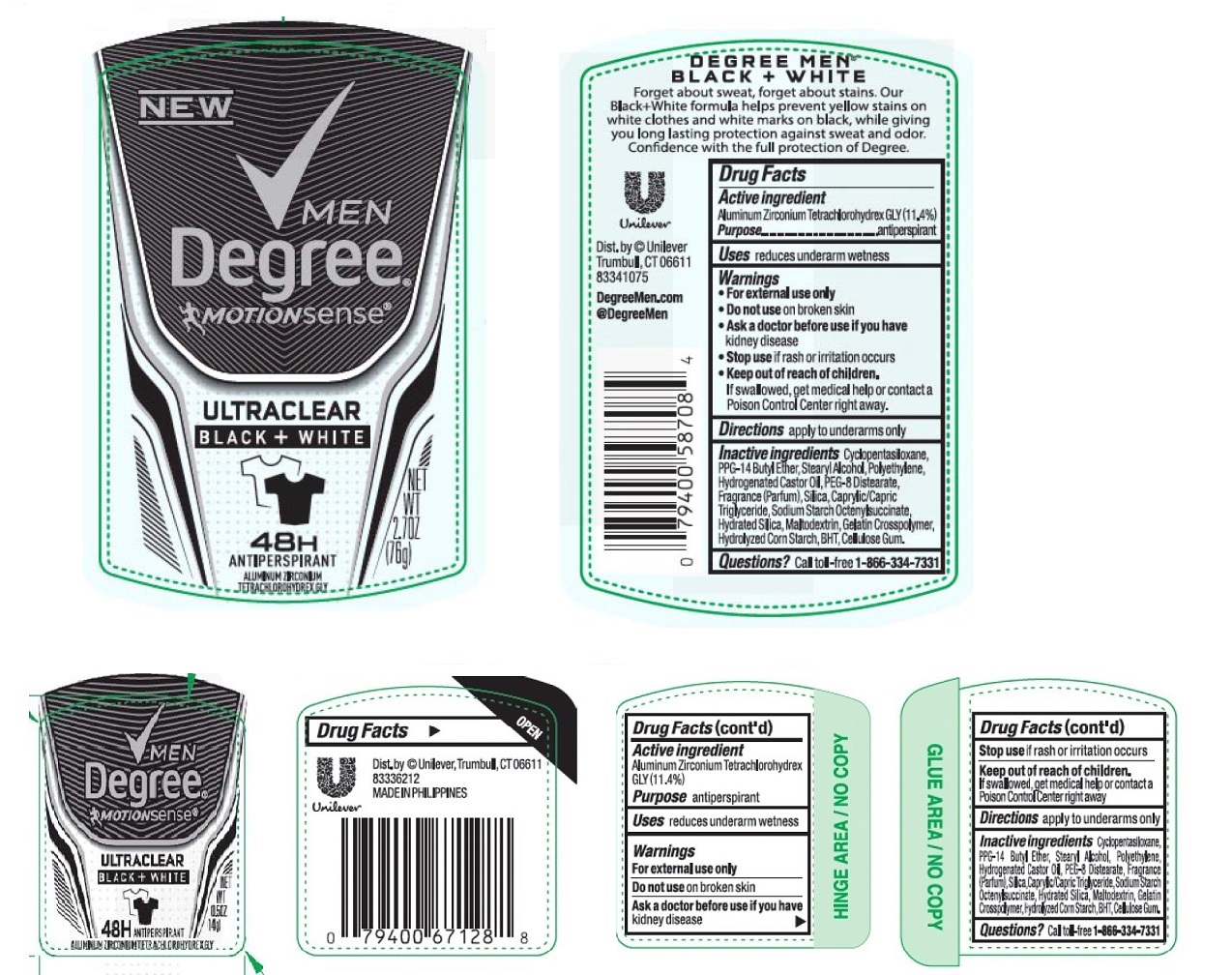 DRUG LABEL: Degree Men
NDC: 64942-1466 | Form: STICK
Manufacturer: Conopco, Inc. d/b/a Unilever
Category: otc | Type: HUMAN OTC DRUG LABEL
Date: 20241024

ACTIVE INGREDIENTS: ALUMINUM ZIRCONIUM TETRACHLOROHYDREX GLY 11.4 g/100 g
INACTIVE INGREDIENTS: CYCLOMETHICONE 5; PPG-14 BUTYL ETHER; STEARYL ALCOHOL; HIGH DENSITY POLYETHYLENE; HYDROGENATED CASTOR OIL; PEG-8 DISTEARATE; SILICON DIOXIDE; MEDIUM-CHAIN TRIGLYCERIDES; HYDRATED SILICA; MALTODEXTRIN; STARCH, CORN; BUTYLATED HYDROXYTOLUENE; CARBOXYMETHYLCELLULOSE SODIUM, UNSPECIFIED FORM

Degree Men - Motionsense UltraClear Black and White 48H Antiperspirant

Active ingredient

Aluminum Zirconium Tetrachlorohydrex GLY (11.4 %)

Purpose

antiperspirant

Uses

reduces underarm wetness

Warnings

- For external use only.
- Do not use on broken skin.
- Ask a doctor before use if you have kidney disease.
- Stop use if rash or irritation occurs.

Keep out of reach of children. If swallowed, get medical help or contact a Poison Control Center right away.

Directions

apply to underarms only

Inactive ingredients

Cyclopentasiloxane, PPG-14 Butyl Ether, Stearyl Alcohol, Polyethylene, Hydrogenated Castor Oil, PEG-8 Distearate, Fragrance (Parfum), Silica, Caprylic/Capric Triglyceride, Sodium Starch Octerylsuccinate, Hydrated Silica, Maltodextrin, Gelatin Crosspolymer, Hydrolyzed Corn Starch, BHT, Cellulose Gum.

Questions?

Call toll-free 1-866-334-7331